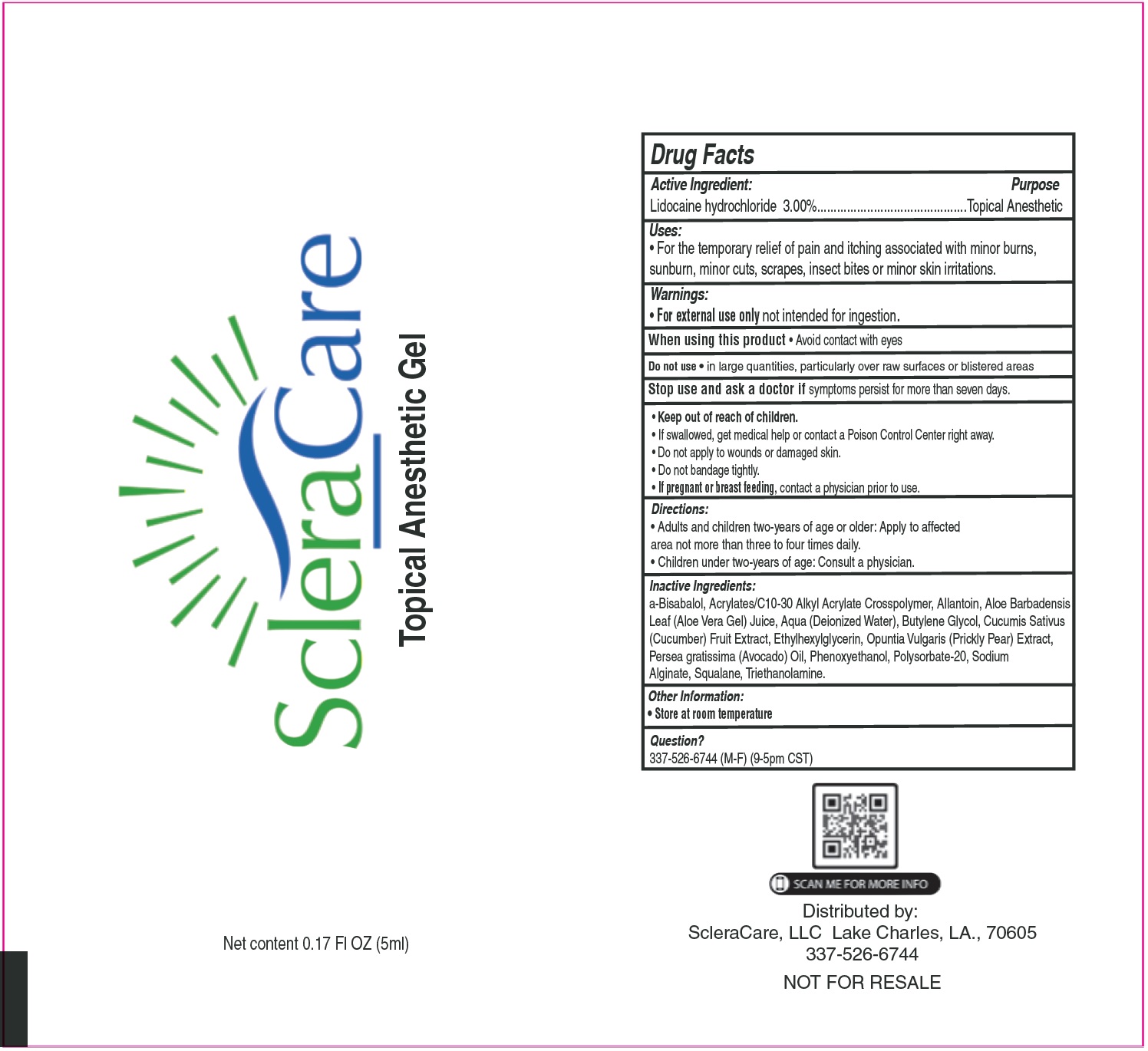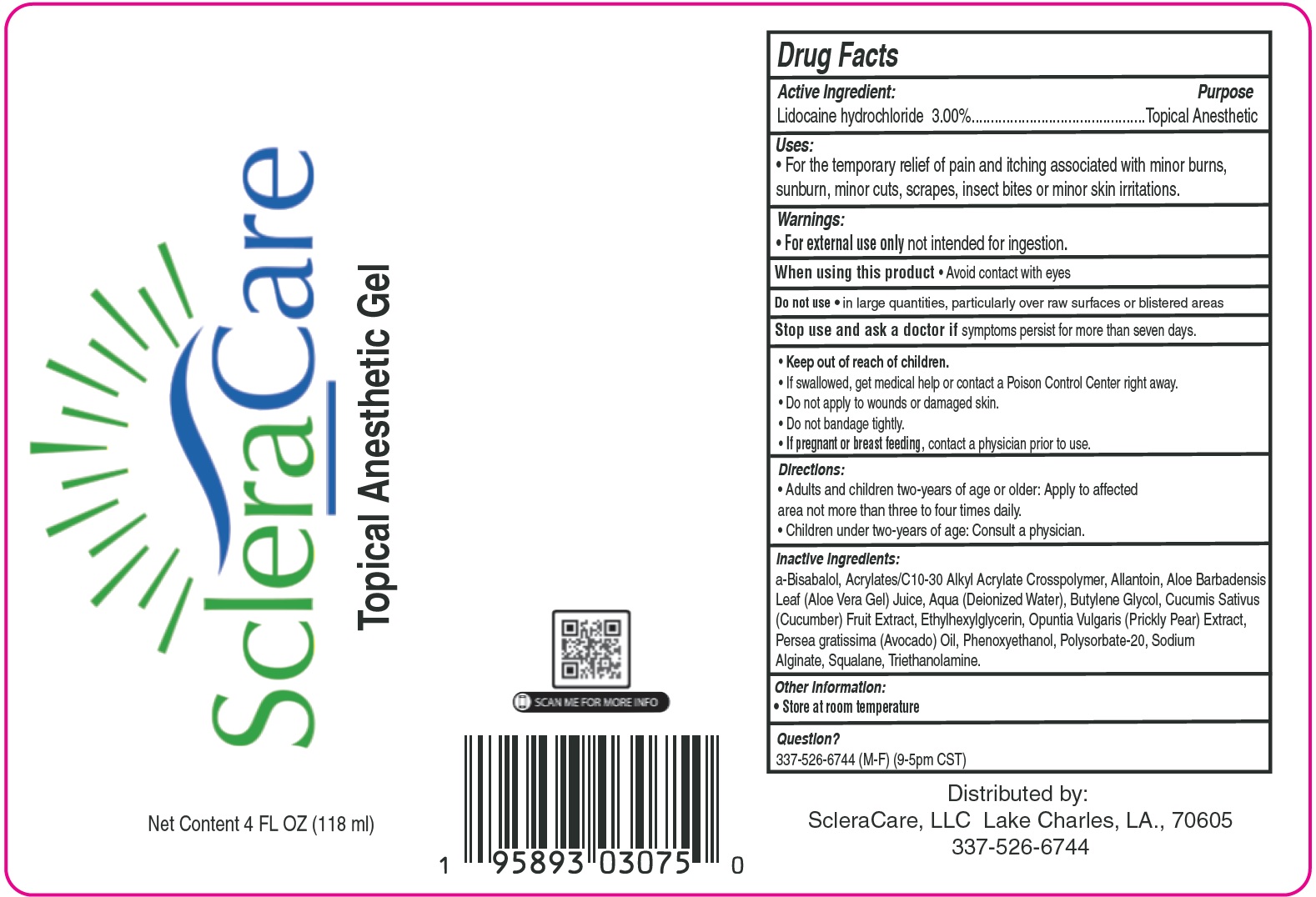 DRUG LABEL: SCLERA CARE Topical Anesthetic Gel
NDC: 73698-281 | Form: GEL
Manufacturer: ScleraCare, LLC
Category: otc | Type: HUMAN OTC DRUG LABEL
Date: 20231105

ACTIVE INGREDIENTS: LIDOCAINE HYDROCHLORIDE 30 mg/1 mL
INACTIVE INGREDIENTS: ALLANTOIN; ALOE VERA LEAF; WATER; BUTYLENE GLYCOL; CUCUMBER; ETHYLHEXYLGLYCERIN; AVOCADO OIL; PHENOXYETHANOL; POLYSORBATE 20; SODIUM ALGINATE; SQUALANE; TROLAMINE

SCLERA CARE Topical Anesthetic Gel

Active Ingredient:

Lidocaine hydrochloride 3.00%

Purpose

Topical Anesthetic

Uses:

• For the temporary relief of pain and itching associated with minor burns, sunburn, minor cuts, scrapes, insect bites or minor skin irritations.

Warnings:

• not intended for ingestion. For external use only

When using this product

• Avoid contact with eyes

Do not use

• in large quantities, particularly over raw surfaces or blistered areas

Stop use and ask a doctor if

symptoms persist for more than seven days.

Keep out of reach of children.

• If swallowed, get medical help or contact a Poison Control Center right away. • Do not apply to wounds or damaged skin. • Do not bandage tightly.

If pregnant or breast feeding,

• contact a physician prior to use.

Directions:

• Adults and children two-years of age or older: Apply to affected area not more than three to four times daily. • Children under two-years of age: Consult a physician.

Inactive Ingredients:

a-Bisabalol, Acrylates/C10-30 Alkyl Acrylate Crosspolymer, Allantoin, Aloe Barbadensis Leaf (Aloe Vera Gel) Juice, Aqua (Deionized Water), Butylene Glycol, Cucumis Sativus (Cucumber) Fruit Extract, Ethylhexylglycerin, Opuntia Vulgaris (Prickly Pear) Extract, Persea gratissima (Avocado) Oil, Phenoxyethanol, Polysorbate-20, Sodium Alginate, Squalane, Triethanolamine.

Other Information:

• Store at room temperature

Question?

337-526-6744 (M-F) (9-5pm CST)